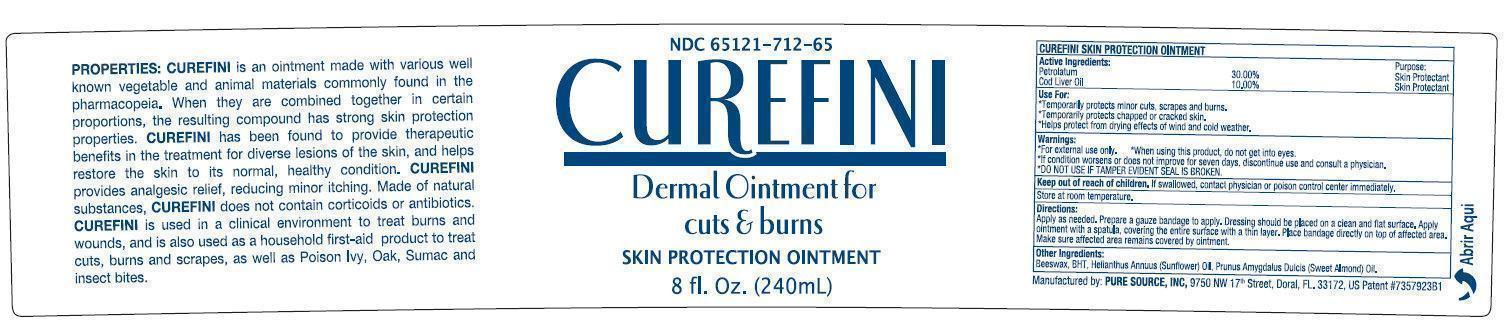 DRUG LABEL: CUREFINI
NDC: 69981-712 | Form: OINTMENT
Manufacturer: Rev Pharma Corp.
Category: otc | Type: HUMAN OTC DRUG LABEL
Date: 20231105

ACTIVE INGREDIENTS: PETROLATUM 300 mg/1 mL; COD LIVER OIL 100 mg/1 mL
INACTIVE INGREDIENTS: YELLOW WAX; BUTYLATED HYDROXYTOLUENE; SUNFLOWER OIL; ALMOND OIL

CUREFINI Dermal Ointment for cuts & burns SKIN PROTECTION OINTMENT

Active Ingredients

- Petrolatum 30.00%

- Cod Liver Oil 10.00%

Purpose

Skin Protectant

Use For:

- Temporarily protects minor cuts, scrapes and burns.
- Temporarily protects chapped or cracked skin.
- Helps protect from drying effects of wind and cold weather.

Warnings

- For external use only
- When using this product, do not get into eyes
- If conditions worsens or does not improve for seven days, discontinue use and consult a physician
- Do not use if tamper evident seal is broken

Keep out of reach of children.

- If swallowed, contact physician or poison control center immediately.

STORAGE AND HANDLING

Store at room temperature.

Directions:

- Apply as needed. Prepare a gauze bandage to apply. Dressing should be placed on a clean and flat surface. Apply ointment with spatula, covering the entire surface with a thin layer. Place bandage directly on top of affected area. Make sure affected area remains covered by ointment.

Other Ingredients:

beeswax, BHT, Sunflower oil, Sweet almond oil